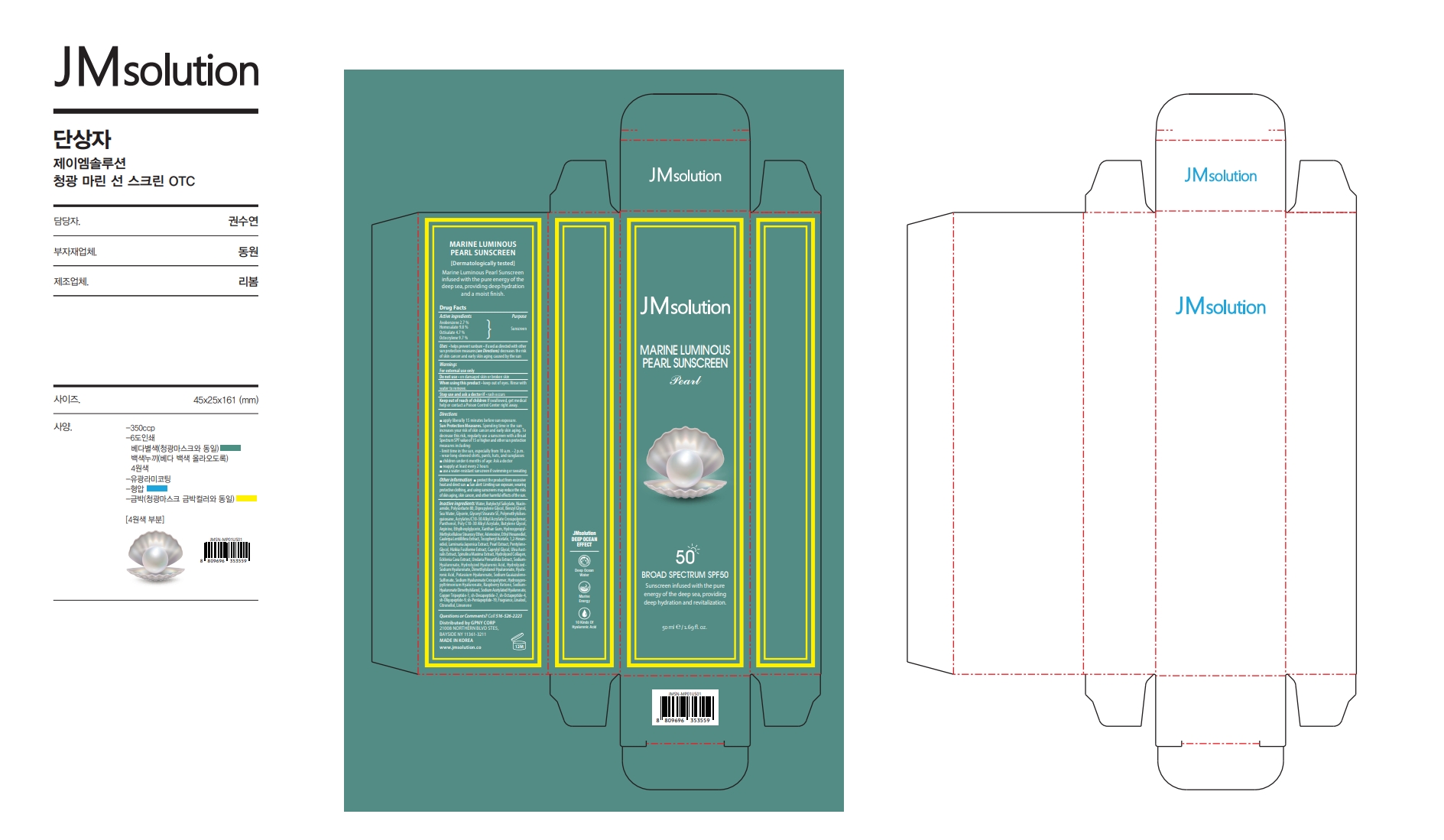 DRUG LABEL: JMSOLUTION MARINE LUMINOUS PEARL SUNSCREEN
NDC: 84754-052 | Form: CREAM
Manufacturer: GPNY CORP
Category: otc | Type: HUMAN OTC DRUG LABEL
Date: 20241106

ACTIVE INGREDIENTS: HOMOSALATE 4.9 g/50 mL; OCTOCRYLENE 4.85 g/50 mL; OCTISALATE 2.35 g/50 mL; AVOBENZONE 1.35 g/50 mL
INACTIVE INGREDIENTS: NIACINAMIDE; BUTYLENE GLYCOL; ETHOHEXADIOL; .ALPHA.-TOCOPHEROL ACETATE; PEA; PENTYLENE GLYCOL; ARTHROSPIRA MAXIMA; POLYSORBATE 80; BENZYL GLYCOL; GLYCERIN; PANTHENOL; ARGININE; XANTHAN GUM; CAULERPA LENTILLIFERA EXTRACT; LAMINARIA JAPONICA EXTRACT; ULVA AUSTRALIS; ECKLONIA CAVA; DIMETHYLSILANOL HYALURONATE; SODIUM GUALENATE; RASPBERRY KETONE; SODIUM ACETYLATED HYALURONATE; BUTYLOCTYL SALICYLATE; 1,2-HEXANEDIOL; CAPRYLYL GLYCOL; BEHENYL ACRYLATE POLYMER; ETHYLHEXYLGLYCERIN; ADENOSINE; SARGASSUM FUSIFORME EXTRACT; UNDARIA PINNATIFIDA; SODIUM HYALURONATE; PREZATIDE COPPER; POLYMETHYLSILSESQUIOXANE (4.5 MICRONS); SODIUM CHLORIDE; GLYCERYL STEARATE SE; .BETA.-CITRONELLOL, (R)-; LIMONENE, (+)-; WATER; DIPROPYLENE GLYCOL; LINALOOL, (+/-)-

JMSOLUTION MARINE LUMINOUS PEARL SUNSCREEN

Active ingredients

Avobenzone 2.7 %
Homosalate 9.8 %
Octisalate 4.7 %
Octocrylene 9.7 %

Purpose

sunscreen

Uses

• helps prevent sunburn • if used as directed with other sun protection measures (see Directions) decreases the risk of skin cancer and early skin aging caused by the sun

Warnings

For external use only

Do not use

• on damaged skin or broken skin

When using this product

• keep out of eyes. Rinse with water to remove.

Stop use and ask a doctor if

• rash occurs

Keep out of reach of children

If swallowed, get medical help or contact a Poison Control Center right away.

Directions

■ apply liberally 15 minutes before sun exposure.
Sun Protection Measures. Spending time in the sun increases your risk of skin cancer and early skin aging. To decrease this risk, regularly use a sunscreen with a Broad Spectrum SPF value of 15 or higher and other sun protection measures including:
• limit time in the sun, especially from 10 a.m. - 2 p.m.
• wear long-sleeved shirts, pants, hats, and sunglasses
■ children under 6 months of age: Ask a doctor
■ reapply at least every 2 hours
■ use a water-resistant sunscreen if swimming or sweating

Other information

■ protect the product from excessive heat and direct sun ■ Sun alert: Limiting sun exposure, wearing protective clothing, and using sunscreens may reduce the risks of skin aging, skin cancer, and other harmful effects of the sun.

Inactive ingredients

Water, Butyloctyl Salicylate, Niacinamide, Polysorbate 80, Dipropylene Glycol, Benzyl Glycol, Sea Water, Glycerin, Glyceryl Stearate SE, Polymethylsilsesquioxane, Acrylates/C10-30 Alkyl Acrylate Crosspolymer, Panthenol, Poly C10-30 Alkyl Acrylate, Butylene Glycol, Arginine, Ethylhexylglycerin, Xanthan Gum, Hydroxypropyl Methylcellulose Stearoxy Ether, Adenosine, Ethyl Hexanediol, Caulerpa Lentillifera Extract, Tocopheryl Acetate, 1,2-Hexanediol, Laminaria Japonica Extract, Pearl Extract, Pentylene Glycol, Hizikia Fusiforme Extract, Caprylyl Glycol, Ulva Australis Extract, Spirulina Maxima Extract, Hydrolyzed Collagen, Ecklonia Cava Extract, Undaria Pinnatifida Extract, Sodium Hyaluronate, Hydrolyzed Hyaluronic Acid, Hydrolyzed Sodium Hyaluronate, Dimethylsilanol Hyaluronate, Hyaluronic Acid, Potassium Hyaluronate, Sodium Guaiazulene Sulfonate, Sodium Hyaluronate Crosspolymer, Hydroxypropyltrimonium Hyaluronate, Raspberry Ketone, Sodium Hyaluronate Dimethylsilanol, Sodium Acetylated Hyaluronate, Copper Tripeptide-1, sh-Decapeptide-7, sh-Octapeptide-4, sh-Oligopeptide-9, sh-Pentapeptide-19, Fragrance, Linalool, Citronellol, Limonene